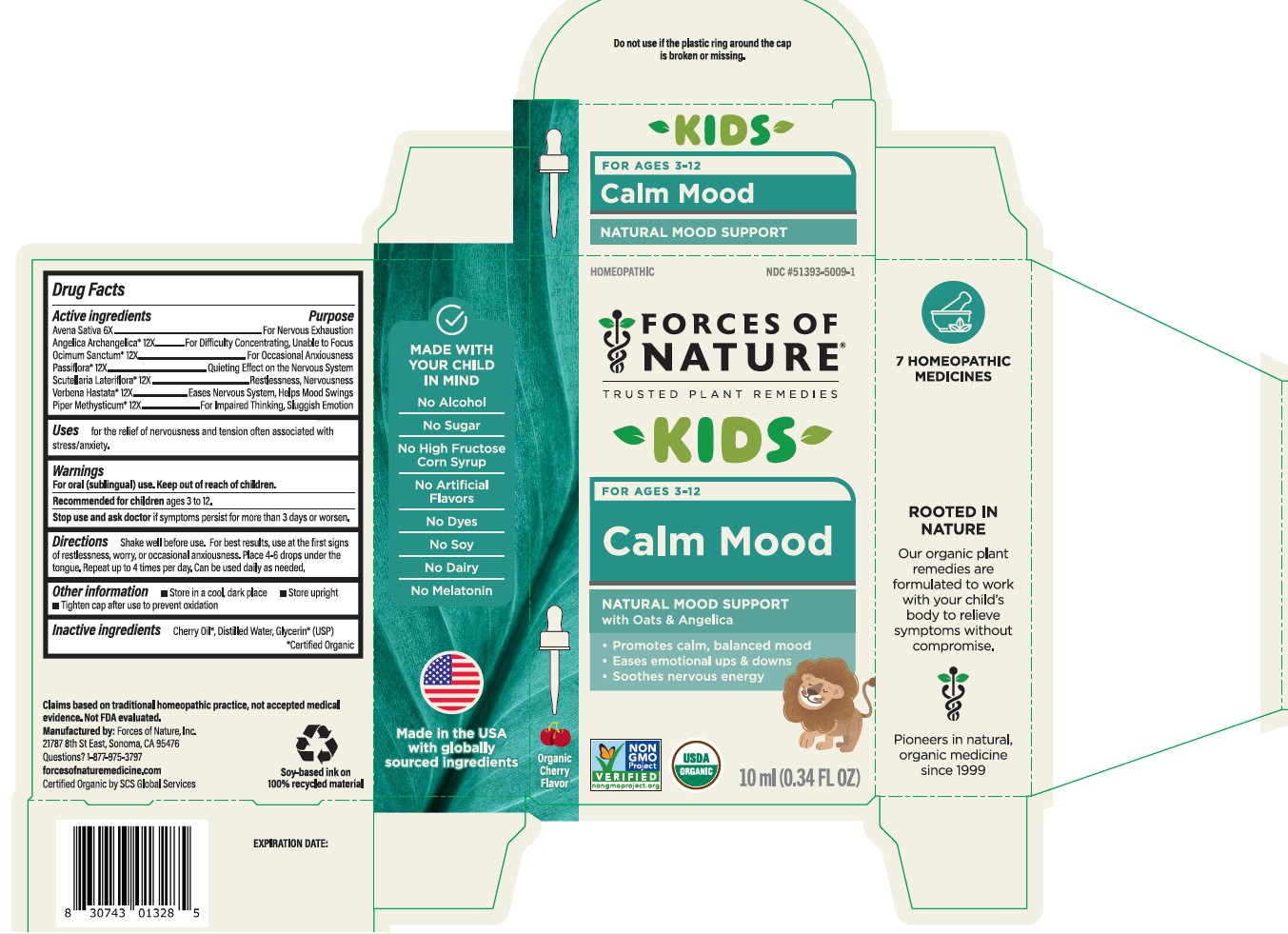 DRUG LABEL: Calm Mood Kids
NDC: 51393-5009 | Form: SOLUTION/ DROPS
Manufacturer: Forces of Nature
Category: homeopathic | Type: HUMAN OTC DRUG LABEL
Date: 20260227

ACTIVE INGREDIENTS: AVENA SATIVA TOP 6 [hp_X]/100 mL; ANGELICA ARCHANGELICA ROOT 12 [hp_X]/100 mL; HOLY BASIL LEAF 12 [hp_X]/100 mL; PASSIFLORA EDULIS FLOWER 12 [hp_X]/100 mL; SCUTELLARIA LATERIFLORA WHOLE 12 [hp_X]/100 mL; VERBENA HASTATA TOP 12 [hp_X]/100 mL; MACROPIPER METHYSTICUM ROOT 12 [hp_X]/100 mL
INACTIVE INGREDIENTS: WATER; GLYCERIN; CLARY SAGE OIL

Calm Mood Kids

Drug Facts

ACTIVE INGREDIENT

Active ingredients | Purpose
Avena sativa [USDA Certified Organic] 12X | For Nervous Exhaustion
Angelica 12X | For Difficulty Concentrating, Unable to Focus
Ocimum 12X | For Anxiety
Passiflora 12X | Quieting Effect on the Nervous System
Scutellaria lateriflora 12X | Restlessness, Nervousness
Verbena 12X | Eases Nervous System, Helps Mood Swings
Piper methysticum 12X | For Impaired Thinking, Sluggish Emotion

Uses

for the relief of nervousness and tension often associated with stress/anxiety.

Warnings

KEEP OUT OF REACH OF CHILDREN

For oral (sublingual) use. Keep out of reach of children.

Recommended for childrenages 3 to 12.

Stop use and ask doctorif symptoms persist for more than 3 days or worsen.

Directions

Shake well before use. For best results, use at the first sign of restlessness, worry, or occasional anxiousness. Place 4 - 6 drops under the tongue. Repeat up to 4 times per day. Can be used daily as needed.

Other information

- Store in a cool, dark place
- Store upright
- Tighten cap after use to prevent oxidation

Inactive ingredients

Cherry Oil*, Distilled Water, Glycerin* (USP)

*Certified Organic

Questions? 1-877-975-3797

forcesofnaturemedicine.com

Manufactured by: Forces of Nature, Inc.

21787 8th Street East, Sonoma, CA 95476

RECENT MAJOR CHANGES

Updated Directions for Use to be clearer including number of uses per day.

PRINCIPAL DISPLAY PANEL - 10 ml Bottle Carton

Homeopathic

NDC #51393-5009-1

FORCES OF NATURE®

TRUSTED PLANT REMEDIES

KIDS

For Ages 3 - 12

Calm Mood

NATURAL MOOD SUPPORT

with Oats & Angelica

- Promotes calm, balanced mood
- Eases emotional ups & downs
- Soothes nervous energy

Organic

Cherry Flavor

NON
GMO
PROJECT
VERIFIED
nongmoproject.org

USDA
ORGANIC

10 ml (0.34 FL OZ)